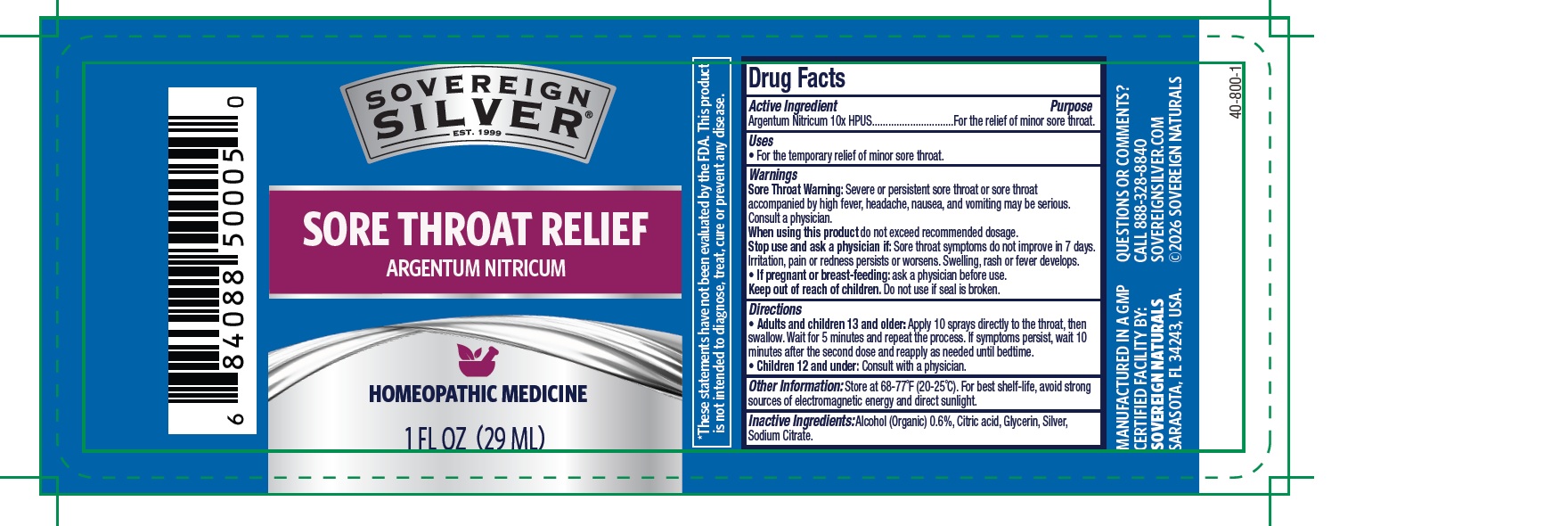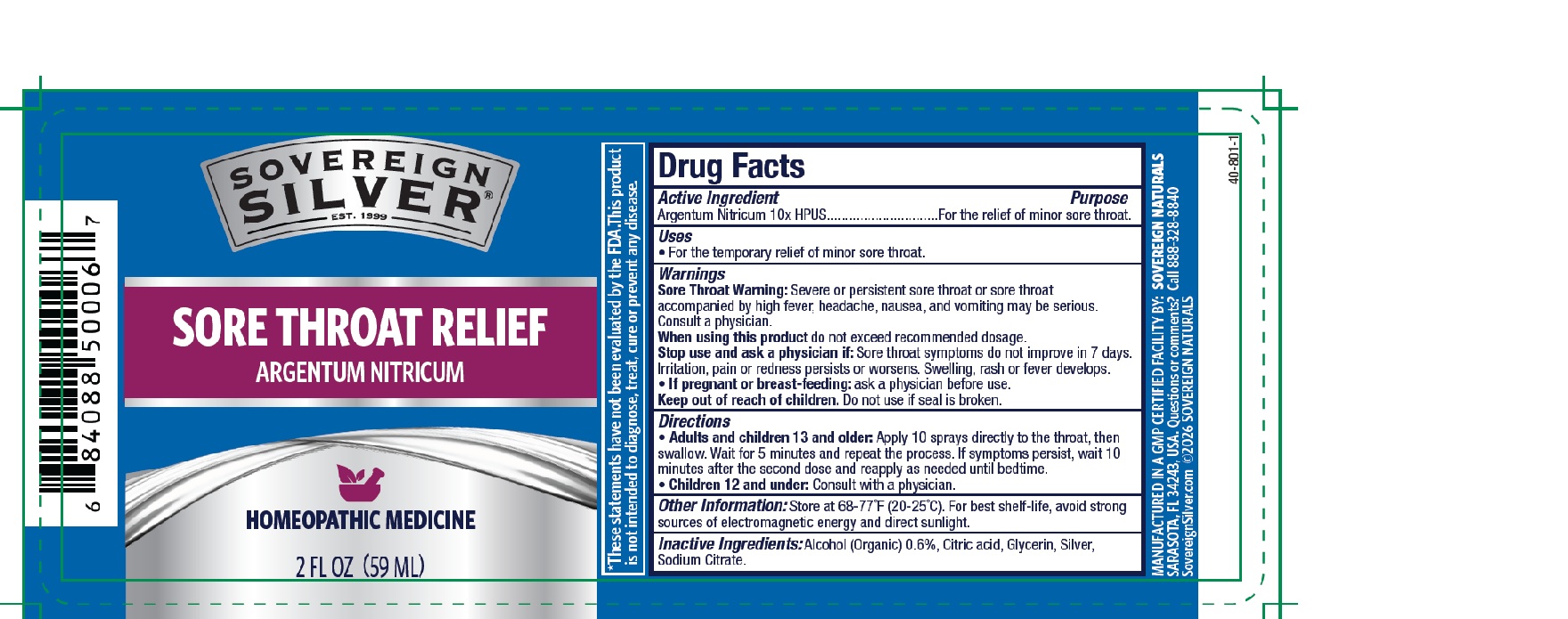 DRUG LABEL: SOVEREIGN SILVER MULTI-SYMPTOM SORE THROAT
NDC: 52166-053 | Form: LIQUID
Manufacturer: Natural Immunogenics Corp.dba SOVEREIGN NATURALS
Category: homeopathic | Type: HUMAN OTC DRUG LABEL
Date: 20251124

ACTIVE INGREDIENTS: SILVER NITRATE 10 [hp_X]/1 mL
INACTIVE INGREDIENTS: ALCOHOL; CITRIC ACID MONOHYDRATE; GLYCERIN; SILVER; SODIUM CITRATE, UNSPECIFIED FORM

Active Ingredient Purpose

Argentum Nitricum 10xHPUS For the temporary relief of minor sore throat

Uses

For the temporary relief of minor sore throat.

Warnings

- Sore Throat Warning: Severe or persistent sore throat or sore throat accompanied by high fever, headache, nausea, and vomiting may be serious. Consult a physician promptly. • Do not use for more than 7 consecutive days.

- When using this productdo not exceed recommended dosage.

- Stop use and ask a physician if: Sore throat symptoms do not improve in 7 days. Irritation, pain or redness persists or worsens.Swelling, rash or fever develops.

- If pregnant or breast-feeding: Ask a physician before use.

- Keep out of reach of children.

- Do not use if seal is broken.

Directions

- Adults and children 13 and older: Apply 10 sprays directly to the throat, then swallow. Wait for 5 minutes and repeat the process. If symptoms persist, wait 10 minutes after the second dose and reapply as needed until bedtime.
- Children 12 and under: Consult with a physician.

Other information

Store at 20-25°C (68-77°F). For best shelf-life avoid strong sources of electromagnetic energy and direct sunlight.

Inactive ingredients

Alcohol (Organic) 0.6%, Citric acid, Glycerin, Silver, Sodium Citrate.

Questions or comments?

888-328-8840